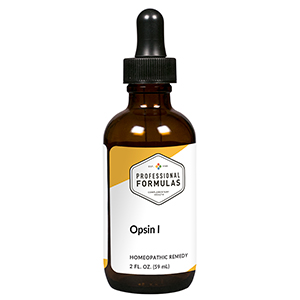 DRUG LABEL: Opsin I
NDC: 63083-6014 | Form: LIQUID
Manufacturer: Professional Complementary Health Formulas
Category: homeopathic | Type: HUMAN OTC DRUG LABEL
Date: 20190815

ACTIVE INGREDIENTS: EPINEPHRINE 6 [hp_X]/59 mL; SILVER NITRATE 6 [hp_X]/59 mL; ARSENIC TRIOXIDE 6 [hp_X]/59 mL; ACTIVATED CHARCOAL 6 [hp_X]/59 mL; HYDRANGEA ARBORESCENS ROOT 6 [hp_X]/59 mL; LIQUID PETROLEUM 6 [hp_X]/59 mL; ACETALDEHYDE 12 [hp_X]/59 mL; COUMARIN 12 [hp_X]/59 mL; GALLIC ACID MONOHYDRATE 12 [hp_X]/59 mL; HISTAMINE DIHYDROCHLORIDE 12 [hp_X]/59 mL; INDOLE-3-CARBINOL 12 [hp_X]/59 mL; YEAST MANNAN 12 [hp_X]/59 mL; RUTIN 12 [hp_X]/59 mL; DEOXYMUTAASPERGILLIC ACID 30 [hp_X]/59 mL
INACTIVE INGREDIENTS: ALCOHOL; WATER

X14

ACTIVE INGREDIENTS

Adrenalinum 6X
Argentum nitricum 6X
Arsenicum album 6X
Carbo vegetabilis 6X
Hydrangea arborescens 6X
Petroleum 6X
Acetaldehyde 12X
Coumarinum 12X
Gallicum acidum 12X
Histaminum hydrochloricum 12X
Indolum 12X
Mannan 12X
Rutin 12X
Aflatoxin 30X

QUESTIONS

Professional Formulas

PO Box 2034 Lake Oswego, OR 97035

INDICATIONS

For the temporary relief of gas, bloating, diarrhea, runny nose, sneezing, itching of the nose or throat, and itchy or watery eyes due to sensitivity to food allergens or autotoxins.*

PURPOSE

*Claims based on traditional homeopathic practice, not accepted medical evidence. Not FDA evaluated.

WARNINGS

In case of overdose, get medical help or contact a poison control center right away.

Keep out of the reach of children.

PREGNANCY OR BREAST FEEDING

If pregnant or breastfeeding, ask a healthcare professional before use.

DIRECTIONS

Place drops under tongue 30 minutes before/after meals. Adults and children 12 years and over: Take 10 drops up to 3 times per day. Consult a physician for use in children under 12 years of age.

OTHER INFORMATION

Tamper resistant. If seal is broken, do not use. After opening, close container tightly and store at room temperature away from heat.

INACTIVE INGREDIENTS

20% ethanol, purified water.

LABEL

Est 1985

Professional Formulas

Complementary Health

Opsin I

Homeopathic Remedy

2 FL. OZ. (59 mL)